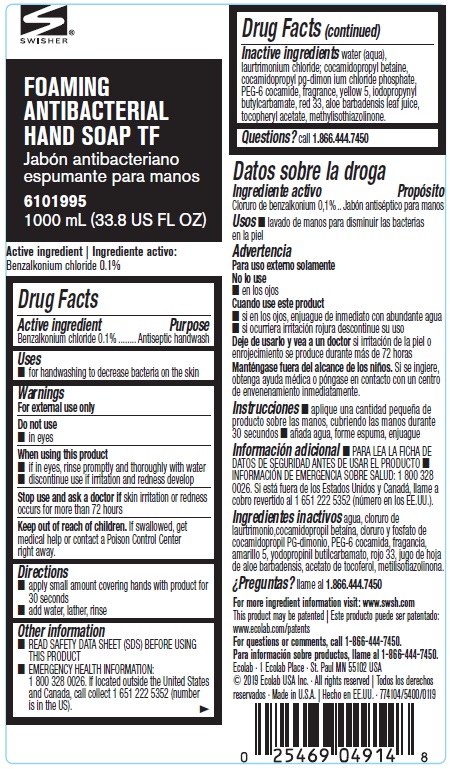 DRUG LABEL: Swisher TF
NDC: 47593-601 | Form: SOLUTION
Manufacturer: Ecolab Inc.
Category: otc | Type: HUMAN OTC DRUG LABEL
Date: 20240805

ACTIVE INGREDIENTS: BENZALKONIUM CHLORIDE 1 mg/1 mL
INACTIVE INGREDIENTS: WATER; LAURTRIMONIUM CHLORIDE; COCAMIDOPROPYL BETAINE; COCAMIDOPROPYL PG-DIMONIUM CHLORIDE PHOSPHATE; PEG-6 COCAMIDE; FD&C YELLOW NO. 5; IODOPROPYNYL BUTYLCARBAMATE; D&C RED NO. 33; ALOE VERA LEAF; .ALPHA.-TOCOPHEROL ACETATE; METHYLISOTHIAZOLINONE

Drug Facts

Active Ingredient

Benzalkonium chloride 0.1%

Purpose

Antiseptic handwash

Uses

- for handwashing to decrease bacteria on the skin

Warning

For external use only

Do not use

- in eyes

When using the product

- if in eyes, rinse promptly and thoroughly with water
- discontinue use if irritation and redness develop

Stop use and ask a physician if skin irritation or redness occurs for more than 72 hours

Keep out of reach of children. If swallowed, get medical help or contact a Poison Control Center right away.

Directions

- apply small amont covering hands with product for 30 seconds
- add water, lather, rinse

Other information

- READ SAFETY DATA SHEET (SDS) BEFORE USING THIS PRODUCT
- EMERGENCY HEALTH INFORMATION:1 800 328 0026. If located outside the United States and Canada, call collect 1 651 222 5352 (number is in the US).

INACTIVE INGREDIENT

Inactive ingredients water (aqua), laurtrimonium chloride; cocamidopropyl betaine, cocamidopropyl pg-dimon ium chloride phosphate, PEG-6 cocamide, fragrance, yellow 5, iodopropynyl butylcarbamate, red 33, aloe barbadensis leaf juice, tocopheryl acetate, methylisothiazolinone.

Questions? call 1.866.444.7450

Representative label and principal display panel

SWISHER

FOAMING

ANTIBACTERIAL

HAND SOAP TF

6101995

1000 mL (33.8 US FL OZ)

Active ingredient:

Benzalkonium chloride 0.1%

For more ingredient information visit: www.swsh.com

This product may be patented: www.ecolab.com/patents

For questions or comments, call 1-866-444-7450.

Ecolab · 1 Ecolab Place · St. Paul MN 55102 USA

© 2019 Ecolab USA Inc. · All rights reserved · Made in U.S.A. · 774104/5400/0119